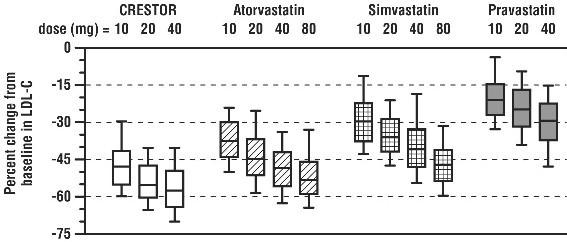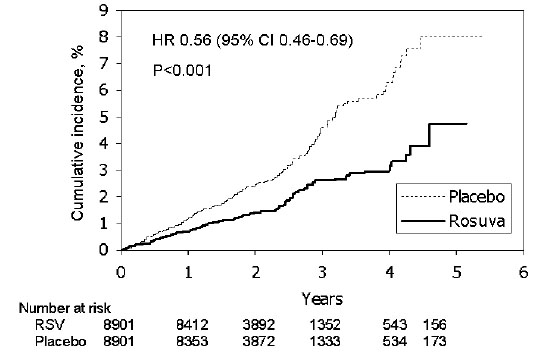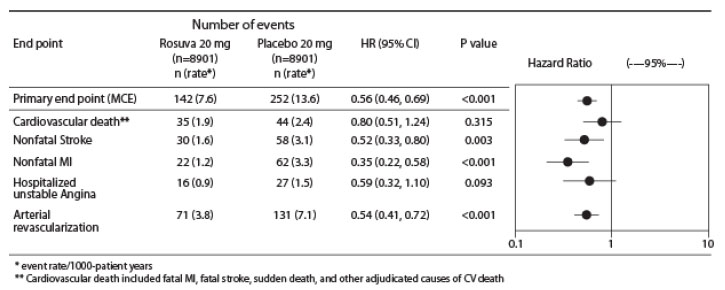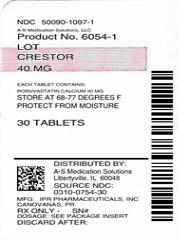 DRUG LABEL: CRESTOR
NDC: 50090-1097 | Form: TABLET, FILM COATED
Manufacturer: A-S Medication Solutions
Category: prescription | Type: HUMAN PRESCRIPTION DRUG LABEL
Date: 20200118

ACTIVE INGREDIENTS: ROSUVASTATIN CALCIUM 40 mg/1 1
INACTIVE INGREDIENTS: LACTOSE MONOHYDRATE; MICROCRYSTALLINE CELLULOSE; TRIBASIC CALCIUM PHOSPHATE; CROSPOVIDONE (15 MPA.S AT 5%); MAGNESIUM STEARATE; HYPROMELLOSE, UNSPECIFIED; TRIACETIN; TITANIUM DIOXIDE; FERRIC OXIDE RED

HIGHLIGHTS OF PRESCRIBING INFORMATION

These highlights do not include all the information needed to use CRESTOR safely and effectively. See full prescribing information for CRESTOR.
CRESTOR (rosuvastatin calcium) tablets
Initial U.S. Approval: 2003

1 INDICATIONS AND USAGE

CRESTOR is an HMG Co-A reductase inhibitor indicated for:

- adult patients with primary hyperlipidemia and mixed dyslipidemia as an adjunct to diet to reduce elevated total-C, LDL-C, ApoB, nonHDL-C, and TG levels and to increase HDL-C (1.1)
- pediatric patients 8 to 17 years of age with heterozygous familial hypercholesterolemia (HeFH) to reduce elevated total-C, LDL-C and ApoB after failing an adequate trial of diet therapy (1.2)
- pediatric patients 7 to 17 years of age with homozygous familial hypercholesterolemia (HoFH) to reduce LDL-C, total-C, nonHDL-C and ApoB as an adjunct to diet, either alone or with other lipid-lowering treatments (1.2)
- adult patients with hypertriglyceridemia as an adjunct to diet (1.3)
- adult patients with primary dysbetalipoproteinemia (Type III hyperlipoproteinemia) as an adjunct to diet (1.4)
- adult patients with homozygous familial hypercholesterolemia (HoFH) to reduce LDL-C, total-C, and ApoB (1.5)
- slowing the progression of atherosclerosis as part of a treatment strategy to lower total-C and LDL-C as an adjunct to diet (1.6)
- risk reduction of MI, stroke, and arterial revascularization procedures in patients without clinically evident CHD, but with multiple risk factors (1.7)

Limitations of use (1.8): CRESTOR has not been studied in Fredrickson Type I and V dyslipidemias.

2 DOSAGE AND ADMINISTRATION

- CRESTOR can be taken with or without food, at any time of day. (2.1)
- Dose range: 5-40 mg once daily. Use 40 mg dose only for patients not reaching LDL-C goal with 20 mg. (2.1)
- Adult HoFH: Starting dose 20 mg/day. (2.1)
- Pediatric patients with HeFH: 5 to 10 mg/day for patients 8 to less than 10 years of age, and 5 to 20 mg/day for patients 10 to 17 years of age. (2.2)
- Pediatric patients with HoFH: 20 mg/day for patients 7 to 17 years of age. (2.2)

3 DOSAGE FORMS AND STRENGTHS

Tablets: 5 mg, 10 mg, 20 mg, and 40 mg (3)

4 CONTRAINDICATIONS

- Known hypersensitivity to product components (4)
- Active liver disease, which may include unexplained persistent elevations in hepatic transaminase levels (4)
- Pregnancy (4, 8.1, 8.3)
- Lactation (4, 8.2)

5 WARNINGS AND PRECAUTIONS

- Skeletal muscle effects (e.g., myopathy and rhabdomyolysis): Risks increase with use of 40 mg dose, advanced age (≥65), hypothyroidism, renal impairment, and combination use with cyclosporine, atazanavir/ritonavir, lopinavir/ritonavir, or simeprevir. Cases of myopathy and rhabdomyolysis with acute renal failure secondary to myoglobinuria have been reported. Advise patients to promptly report to their physician unexplained and/or persistent muscle pain, tenderness, or weakness and discontinue CRESTOR if signs or symptoms appear. (5.1, 7.5, 7.6)
- Liver enzyme abnormalities: Persistent elevations in hepatic transaminases can occur. Perform liver enzyme tests before initiating therapy and as clinically indicated thereafter. (5.2)

6 ADVERSE REACTIONS

Most frequent adverse reactions (rate >2%) are headache, myalgia, abdominal pain, asthenia, and nausea. (6.1)

To report SUSPECTED ADVERSE REACTIONS, contact AstraZeneca at 1-800-236-9933 or FDA at 1-800-FDA-1088 or www.fda.gov/medwatch.

7 DRUG INTERACTIONS

- Cyclosporine: Combination increases rosuvastatin exposure. Limit CRESTOR dose to 5 mg once daily. (2.4, 5.1, 7.1, 12.3)
- Gemfibrozil: Combination should be avoided. If used together, limit CRESTOR dose to 10 mg once daily. (2.4, 5.1, 7.2)
- Atazanavir/ritonavir, lopinavir/ritonavir, or simeprevir: Combination increases rosuvastatin exposure. Limit CRESTOR dose to 10 mg once daily. (2.4, 5.1, 7.3, 12.3)
- Coumarin anticoagulants: Combination prolongs INR. Achieve stable INR prior to starting CRESTOR. Monitor INR frequently until stable upon initiation or alteration of CRESTOR therapy. (5.3, 7.4)
- Concomitant lipid-lowering therapies: Use with fibrates or lipid-modifying doses (≥1 g/day) of niacin increases the risk of adverse skeletal muscle effects. Caution should be used when prescribing with CRESTOR. (5.1, 7.5, 7.6)

8 USE IN SPECIFIC POPULATIONS

- Females of reproductive potential: Advise females of reproductive potential to use effective contraception during treatment with CRESTOR. (8.3)
- Severe renal impairment (not on hemodialysis): Starting dose is 5 mg, not to exceed 10 mg. (2.5, 5.1, 8.6)
- Asian population: Consider 5 mg starting dose. (2.3, 8.8)

FULL PRESCRIBING INFORMATION

1 INDICATIONS AND USAGE

1.1 Hyperlipidemia and Mixed Dyslipidemia

CRESTOR is indicated as adjunctive therapy to diet to reduce elevated Total-C, LDL-C, ApoB, nonHDL‑C, and triglycerides and to increase HDL‑C in adult patients with primary hyperlipidemia or mixed dyslipidemia. Lipid-altering agents should be used in addition to a diet restricted in saturated fat and cholesterol when response to diet and nonpharmacological interventions alone has been inadequate.

1.2 Pediatric Patients with Familial Hypercholesterolemia

CRESTOR is indicated as an adjunct to diet to:

- reduce Total-C, LDL-C and ApoB levels in children and adolescents 8 to 17 years of age with heterozygous familial hypercholesterolemia if after an adequate trial of diet therapy the following findings are present: LDL-C >190 mg/dL, or >160 mg/dL along with a positive family history of premature cardiovascular disease (CVD) or two or more other CVD risk factors.
- reduce LDL-C, Total-C, nonHDL-C and ApoB in children and adolescents 7 to 17 years of age with homozygous familial hypercholesterolemia, either alone or with other lipid-lowering treatments (e.g., LDL apheresis).

1.3 Hypertriglyceridemia

CRESTOR is indicated as adjunctive therapy to diet for the treatment of adult patients with hypertriglyceridemia.

1.4 Primary Dysbetalipoproteinemia (Type III Hyperlipoproteinemia)

CRESTOR is indicated as an adjunct to diet for the treatment of adult patients with primary dysbetalipoproteinemia (Type III Hyperlipoproteinemia).

1.5 Adult Patients with Homozygous Familial Hypercholesterolemia

CRESTOR is indicated as adjunctive therapy to other lipid-lowering treatments (e.g., LDL apheresis) or alone if such treatments are unavailable to reduce LDL‑C, Total‑C, and ApoB in adult patients with homozygous familial hypercholesterolemia.

1.6 Slowing of the Progression of Atherosclerosis

CRESTOR is indicated as adjunctive therapy to diet to slow the progression of atherosclerosis in adult patients as part of a treatment strategy to lower Total‑C and LDL‑C to target levels.

1.7 Primary Prevention of Cardiovascular Disease

In individuals without clinically evident coronary heart disease but with an increased risk of cardiovascular disease based on age ≥50 years old in men and ≥60 years old in women, hsCRP ≥2 mg/L, and the presence of at least one additional cardiovascular disease risk factor such as hypertension, low HDL‑C, smoking, or a family history of premature coronary heart disease, CRESTOR is indicated to:

- reduce the risk of stroke
- reduce the risk of myocardial infarction
- reduce the risk of arterial revascularization procedures

1.8 Limitations of Use

CRESTOR has not been studied in Fredrickson Type I and V dyslipidemias.

2 DOSAGE AND ADMINISTRATION

2.1 General Dosing Information

The dose range for CRESTOR in adults is 5 to 40 mg orally once daily. The usual starting dose is 10 to 20 mg once daily. The usual starting dose in adult patients with homozygous familial hypercholesterolemia is 20 mg once daily.

The maximum CRESTOR dose of 40 mg should be used only for those patients who have not achieved their LDL-C goal utilizing the 20 mg dose [see Warnings and Precautions (5.1)].

CRESTOR can be administered as a single dose at any time of day, with or without food. The tablet should be swallowed whole.

When initiating CRESTOR therapy or switching from another HMG‑CoA reductase inhibitor therapy, the appropriate CRESTOR starting dose should first be utilized, and only then titrated according to the patient’s response and individualized goal of therapy.

After initiation or upon titration of CRESTOR, lipid levels should be analyzed within 2 to 4 weeks and the dosage adjusted accordingly.

2.2 Pediatric Dosing

In heterozygous familial hypercholesterolemia, the recommended dose range is 5 to 10 mg orally once daily in patients 8 to less than 10 years of age, and 5 to 20 mg orally once daily in patients 10 to 17 years of age.

In homozygous familial hypercholesterolemia, the recommended dose is 20 mg orally once daily in patients 7 to 17 years of age.

2.3 Dosing in Asian Patients

In Asian patients, consider initiation of CRESTOR therapy with 5 mg once daily due to increased rosuvastatin plasma concentrations. The increased systemic exposure should be taken into consideration when treating Asian patients not adequately controlled at doses up to 20 mg/day [see Use in Specific Populations (8.8) and Clinical Pharmacology (12.3)].

2.4 Use with Concomitant Therapy

Patients taking cyclosporine

The dose of CRESTOR should not exceed 5 mg once daily [see Warnings and Precautions (5.1), Drug Interactions (7.1) and Clinical Pharmacology (12.3)].

Patients taking gemfibrozil

Avoid concomitant use of CRESTOR with gemfibrozil. If concomitant use cannot be avoided, initiate CRESTOR at 5 mg once daily. The dose of CRESTOR should not exceed 10 mg once daily [see Warnings and Precautions (5.1), Drug Interactions (7.2) and Clinical Pharmacology (12.3)].

Patients taking atazanavir and ritonavir, lopinavir and ritonavir, or simeprevir

Initiate CRESTOR therapy with 5 mg once daily. The dose of CRESTOR should not exceed 10 mg once daily [see Warnings and Precautions (5.1), Drug Interactions (7.3) and Clinical Pharmacology (12.3)].

2.5 Dosing in Patients with Severe Renal Impairment

For patients with severe renal impairment (CLcr <30 mL/min/1.73 m^2) not on hemodialysis, dosing of CRESTOR should be started at 5 mg once daily and not exceed 10 mg once daily [see Use in Specific Populations (8.6) and Clinical Pharmacology (12.3)].

3 DOSAGE FORMS AND STRENGTHS

5 mg: Yellow, round, biconvex, coated tablets. Debossed “CRESTOR” and “5” on one side of the tablet.

10 mg: Pink, round, biconvex, coated tablets. Debossed “CRESTOR” and “10” on one side of the tablet.

20 mg: Pink, round, biconvex, coated tablets. Debossed “CRESTOR” and “20” on one side of the tablet.

40 mg: Pink, oval, biconvex, coated tablets. Debossed “CRESTOR” on one side and “40” on the other side of the tablet.

4 CONTRAINDICATIONS

CRESTOR is contraindicated in the following conditions:

- Patients with a known hypersensitivity to any component of this product. Hypersensitivity reactions including rash, pruritus, urticaria, and angioedema have been reported with CRESTOR [see Adverse Reactions (6.1)].
- Patients with active liver disease, which may include unexplained persistent elevations of hepatic transaminase levels [see Warnings and Precautions (5.2)].
- Pregnancy [see Use in Specific Populations (8.1, 8.3)].
- Lactation. Limited data indicate that CRESTOR is present in human milk. Because statins have the potential for serious adverse reactions in nursing infants, women who require CRESTOR treatment should not breastfeed their infants [see Use in Specific Populations (8.2)].

5 WARNINGS AND PRECAUTIONS

5.1 Skeletal Muscle Effects

Cases of myopathy and rhabdomyolysis with acute renal failure secondary to myoglobinuria have been reported with HMG-CoA reductase inhibitors, including CRESTOR. These risks can occur at any dose level, but are increased at the highest dose (40 mg).

CRESTOR should be prescribed with caution in patients with predisposing factors for myopathy (e.g., age ≥65 years, inadequately treated hypothyroidism, renal impairment).

The risk of myopathy during treatment with CRESTOR may be increased with concurrent administration of some other lipid-lowering therapies (fibrates or niacin), gemfibrozil, cyclosporine, atazanavir/ritonavir, lopinavir/ritonavir, or simeprevir [see Dosage and Administration (2) and Drug Interactions (7)]. Cases of myopathy, including rhabdomyolysis, have been reported with HMG-CoA reductase inhibitors, including rosuvastatin, coadministered with colchicine, and caution should be exercised when prescribing CRESTOR with colchicine [see Drug Interactions (7.7)].

CRESTOR therapy should be discontinued if markedly elevated creatine kinase levels occur or myopathy is diagnosed or suspected. CRESTOR therapy should also be temporarily withheld in any patient with an acute, serious condition suggestive of myopathy or predisposing to the development of renal failure secondary to rhabdomyolysis (e.g., sepsis, hypotension, dehydration, major surgery, trauma, severe metabolic, endocrine, and electrolyte disorders, or uncontrolled seizures).

There have been rare reports of immune-mediated necrotizing myopathy (IMNM), an autoimmune myopathy, associated with statin use. IMNM is characterized by: proximal muscle weakness and elevated serum creatine kinase, which persist despite discontinuation of statin treatment; muscle biopsy showing necrotizing myopathy without significant inflammation; improvement with immunosuppressive agents.

All patients should be advised to promptly report to their physician unexplained muscle pain, tenderness, or weakness, particularly if accompanied by malaise or fever or if muscle signs and symptoms persist after discontinuing CRESTOR.

5.2 Liver Enzyme Abnormalities

It is recommended that liver enzyme tests be performed before the initiation of CRESTOR, and if signs or symptoms of liver injury occur.

Increases in serum transaminases [AST (SGOT) or ALT (SGPT)] have been reported with HMG‑CoA reductase inhibitors, including CRESTOR. In most cases, the elevations were transient and resolved or improved on continued therapy or after a brief interruption in therapy. There were two cases of jaundice, for which a relationship to CRESTOR therapy could not be determined, which resolved after discontinuation of therapy. There were no cases of liver failure or irreversible liver disease in these trials.

In a pooled analysis of placebo-controlled trials, increases in serum transaminases to >3 times the upper limit of normal occurred in 1.1% of patients taking CRESTOR versus 0.5% of patients treated with placebo.

There have been rare postmarketing reports of fatal and non-fatal hepatic failure in patients taking statins, including rosuvastatin. If serious liver injury with clinical symptoms and/or hyperbilirubinemia or jaundice occurs during treatment with CRESTOR, promptly interrupt therapy. If an alternate etiology is not found, do not restart CRESTOR.

CRESTOR should be used with caution in patients who consume substantial quantities of alcohol and/or have a history of chronic liver disease [see Clinical Pharmacology (12.3)]. Active liver disease, which may include unexplained persistent transaminase elevations, is a contraindication to the use of CRESTOR [see Contraindications (4)].

5.3 Concomitant Coumarin Anticoagulants

Caution should be exercised when anticoagulants are given in conjunction with CRESTOR because of its potentiation of the effect of coumarin-type anticoagulants in prolonging the prothrombin time/INR. In patients taking coumarin anticoagulants and CRESTOR concomitantly, INR should be determined before starting CRESTOR and frequently enough during early therapy to ensure that no significant alteration of INR occurs [see Drug Interactions (7.4)].

5.4 Proteinuria and Hematuria

In the CRESTOR clinical trial program, dipstick-positive proteinuria and microscopic hematuria were observed among CRESTOR treated patients. These findings were more frequent in patients taking CRESTOR 40 mg, when compared to lower doses of CRESTOR or comparator HMG‑CoA reductase inhibitors, though it was generally transient and was not associated with worsening renal function. Although the clinical significance of this finding is unknown, a dose reduction should be considered for patients on CRESTOR therapy with unexplained persistent proteinuria and/or hematuria during routine urinalysis testing.

5.5 Endocrine Effects

Increases in HbA1c and fasting serum glucose levels have been reported with HMG‑CoA reductase inhibitors, including CRESTOR. Based on clinical trial data with CRESTOR, in some instances these increases may exceed the threshold for the diagnosis of diabetes mellitus [see Adverse Reactions (6.1)].

Although clinical studies have shown that CRESTOR alone does not reduce basal plasma cortisol concentration or impair adrenal reserve, caution should be exercised if CRESTOR is administered concomitantly with drugs that may decrease the levels or activity of endogenous steroid hormones such as ketoconazole, spironolactone, and cimetidine.

6 ADVERSE REACTIONS

The following serious adverse reactions are discussed in greater detail in other sections of the label:

- Rhabdomyolysis with myoglobinuria and acute renal failure and myopathy (including myositis) [see Warnings and Precautions (5.1)]
- Liver enzyme abnormalities [see Warnings and Precautions (5.2)]

6.1 Clinical Studies Experience

Because clinical studies are conducted under widely varying conditions, adverse reaction rates observed in the clinical studies of a drug cannot be directly compared to rates in the clinical studies of another drug and may not reflect the rates observed in clinical practice.

In the CRESTOR controlled clinical trials database (placebo or active-controlled) of 5394 patients with a mean treatment duration of 15 weeks, 1.4% of patients discontinued due to adverse reactions. The most common adverse reactions that led to treatment discontinuation were:

- myalgia
- abdominal pain
- nausea

The most commonly reported adverse reactions (incidence ≥2%) in the CRESTOR controlled clinical trial database of 5394 patients were:

- headache
- myalgia
- abdominal pain
- asthenia
- nausea

Adverse reactions reported in ≥2% of patients in placebo-controlled clinical studies and at a rate greater than placebo are shown in Table 1. These studies had a treatment duration of up to 12 weeks.

Table 1. Adverse Reactions [Adverse reactions by COSTART preferred term.] Reported in ≥2% of Patients Treated with CRESTOR and > Placebo in Placebo-Controlled Trials (% of Patients)
Adverse Reactions | CRESTOR; 5 mg; N=291 | CRESTOR; 10 mg; N=283 | CRESTOR; 20 mg; N=64 | CRESTOR; 40 mg; N=106 | Total CRESTOR; 5 mg‑40 mg; N=744 | Placebo; N=382
Headache | 5.5 | 4.9 | 3.1 | 8.5 | 5.5 | 5.0
Nausea | 3.8 | 3.5 | 6.3 | 0 | 3.4 | 3.1
Myalgia | 3.1 | 2.1 | 6.3 | 1.9 | 2.8 | 1.3
Asthenia | 2.4 | 3.2 | 4.7 | 0.9 | 2.7 | 2.6
Constipation | 2.1 | 2.1 | 4.7 | 2.8 | 2.4 | 2.4

Other adverse reactions reported in clinical studies were abdominal pain, dizziness, hypersensitivity (including rash, pruritus, urticaria, and angioedema) and pancreatitis. The following laboratory abnormalities have also been reported: dipstick-positive proteinuria and microscopic hematuria [see Warnings and Precautions (5.4)]; elevated creatine phosphokinase, transaminases, glucose, glutamyl transpeptidase, alkaline phosphatase, and bilirubin; and thyroid function abnormalities.

In the METEOR study, involving 981 participants treated with rosuvastatin 40 mg (n=700) or placebo (n=281) with a mean treatment duration of 1.7 years, 5.6% of subjects treated with CRESTOR versus 2.8% of placebo-treated subjects discontinued due to adverse reactions. The most common adverse reactions that led to treatment discontinuation were: myalgia, hepatic enzyme increased, headache, and nausea [see Clinical Studies (14.8)].

Adverse reactions reported in ≥2% of patients and at a rate greater than placebo are shown in Table 2.

Table 2. Adverse Reactions [Adverse reactions by MedDRA preferred term.] Reported in ≥2% of Patients Treated with CRESTOR and > Placebo in the METEOR Trial (% of Patients)
Adverse Reactions | CRESTOR 40 mg N=700 | Placebo N=281
Myalgia | 12.7 | 12.1
Arthralgia | 10.1 | 7.1
Headache | 6.4 | 5.3
Dizziness | 4.0 | 2.8
Increased CPK | 2.6 | 0.7
Abdominal pain | 2.4 | 1.8
ALT >3x ULN [Frequency recorded as abnormal laboratory value.] | 2.2 | 0.7

In the JUPITER study, 17,802 participants were treated with rosuvastatin 20 mg (n=8901) or placebo (n=8901) for a mean duration of 2 years. A higher percentage of rosuvastatin-treated patients versus placebo-treated patients, 6.6% and 6.2%, respectively, discontinued study medication due to an adverse event, irrespective of treatment causality. Myalgia was the most common adverse reaction that led to treatment discontinuation.

In JUPITER, there was a significantly higher frequency of diabetes mellitus reported in patients taking rosuvastatin (2.8%) versus patients taking placebo (2.3%). Mean HbA1c was significantly increased by 0.1% in rosuvastatin-treated patients compared to placebo-treated patients. The number of patients with a HbA1c >6.5% at the end of the trial was significantly higher in rosuvastatin-treated versus placebo-treated patients [see Warnings and Precautions (5.5) and Clinical Studies (14.9)].

Adverse reactions reported in ≥2% of patients and at a rate greater than placebo are shown in Table 3.

Table 3. Adverse Reactions [Treatment-emergent adverse reactions by MedDRA preferred term.] Reported in ≥2% of Patients Treated with CRESTOR and > Placebo in the JUPITER Trial (% of Patients)
Adverse Reactions | CRESTOR 20 mg; N=8901 | Placebo; N=8901
Myalgia | 7.6 | 6.6
Arthralgia | 3.8 | 3.2
Constipation | 3.3 | 3.0
Diabetes mellitus | 2.8 | 2.3
Nausea | 2.4 | 2.3

Pediatric Patients with Heterozygous Familial Hypercholesterolemia

In a 12-week controlled study in boys and postmenarcheal girls 10 to 17 years of age with heterozygous familial hypercholesterolemia with CRESTOR 5 to 20 mg daily [see Use in Specific Populations (8.4) and Clinical Studies (14.7)], elevations in serum creatine phosphokinase (CK) >10 x ULN were observed more frequently in rosuvastatin compared with placebo-treated children. Four of 130 (3%) children treated with rosuvastatin (2 treated with 10 mg and 2 treated with 20 mg) had increased CK >10 x ULN, compared to 0 of 46 children on placebo.

6.2 Postmarketing Experience

The following adverse reactions have been identified during postapproval use of CRESTOR: arthralgia, fatal and non-fatal hepatic failure, hepatitis, jaundice, thrombocytopenia, depression, sleep disorders (including insomnia and nightmares), peripheral neuropathy, interstitial lung disease and gynecomastia. Because these reactions are reported voluntarily from a population of uncertain size, it is not always possible to reliably estimate their frequency or establish a causal relationship to drug exposure.

There have been rare reports of immune-mediated necrotizing myopathy associated with statin use [see Warnings and Precautions (5.1)].

There have been rare postmarketing reports of cognitive impairment (e.g., memory loss, forgetfulness, amnesia, memory impairment, and confusion) associated with statin use. These cognitive issues have been reported for all statins. The reports are generally nonserious, and reversible upon statin discontinuation, with variable times to symptom onset (1 day to years) and symptom resolution (median of 3 weeks).

7 DRUG INTERACTIONS

7.1 Cyclosporine

Cyclosporine increased rosuvastatin exposure and may result in increased risk of myopathy. Therefore, in patients taking cyclosporine, the dose of CRESTOR should not exceed 5 mg once daily [see Dosage and Administration (2.4), Warnings and Precautions (5.1) and Clinical Pharmacology (12.3)].

7.2 Gemfibrozil

Gemfibrozil significantly increased rosuvastatin exposure. Due to an observed increased risk of myopathy/rhabdomyolysis, combination therapy with CRESTOR and gemfibrozil should be avoided. If used together, the dose of CRESTOR should not exceed 10 mg once daily [see Clinical Pharmacology (12.3)].

7.3 Protease Inhibitors

Coadministration of rosuvastatin with certain protease inhibitors has differing effects on rosuvastatin exposure and may increase risk of myopathy. Simeprevir, which is a hepatitis C virus (HCV) protease inhibitor, or combinations of atazanavir/ritonavir or lopinavir/ritonavir, which are HIV-1 protease inhibitors, increase rosuvastatin exposure [see Table 4 – Clinical Pharmacology (12.3)]. For these protease inhibitors, the dose of CRESTOR should not exceed 10 mg once daily. The combinations of fosamprenavir/ritonavir or tipranavir/ritonavir, which are HIV-1 protease inhibitors, produce little or no change in rosuvastatin exposure. Caution should be exercised when rosuvastatin is coadministered with protease inhibitors [see Dosage and Administration (2.4), Warnings and Precautions (5.1) and Clinical Pharmacology (12.3)].

7.4 Coumarin Anticoagulants

CRESTOR significantly increased INR in patients receiving coumarin anticoagulants. Therefore, caution should be exercised when coumarin anticoagulants are given in conjunction with CRESTOR. In patients taking coumarin anticoagulants and CRESTOR concomitantly, INR should be determined before starting CRESTOR and frequently enough during early therapy to ensure that no significant alteration of INR occurs [see Warnings and Precautions (5.3) and Clinical Pharmacology (12.3)].

7.5 Niacin

The risk of skeletal muscle effects may be enhanced when CRESTOR is used in combination with lipid-modifying doses (≥1 g/day) of niacin; caution should be used when prescribing with CRESTOR [see Warnings and Precautions (5.1)].

7.6 Fenofibrate

When CRESTOR was coadministered with fenofibrate, no clinically significant increase in the AUC of rosuvastatin or fenofibrate was observed. Because it is known that the risk of myopathy during treatment with HMG-CoA reductase inhibitors is increased with concomitant use of fenofibrates, caution should be used when prescribing fenofibrates with CRESTOR [see Warnings and Precautions (5.1) and Clinical Pharmacology (12.3)].

7.7 Colchicine

Cases of myopathy, including rhabdomyolysis, have been reported with HMG‑CoA reductase inhibitors, including rosuvastatin, coadministered with colchicine, and caution should be exercised when prescribing CRESTOR with colchicine [see Warnings and Precautions (5.1)].

8 USE IN SPECIFIC POPULATIONS

8.1 Pregnancy

Risk Summary

CRESTOR is contraindicated for use in pregnant women since safety in pregnant women has not been established and there is no apparent benefit to therapy with CRESTOR during pregnancy. Because HMG-CoA reductase inhibitors decrease cholesterol synthesis and possibly the synthesis of other biologically active substances derived from cholesterol, CRESTOR may cause fetal harm when administered to pregnant women. CRESTOR should be discontinued as soon as pregnancy is recognized [see Contraindications (4)]. Limited published data on the use of rosuvastatin are insufficient to determine a drug-associated risk of major congenital malformations or miscarriage. In animal reproduction studies, there were no adverse developmental effects with oral administration of rosuvastatin during organogenesis at systemic exposures equivalent to a maximum recommended human dose (MRHD) of 40 mg/day in rats or rabbits (based on AUC and body surface area, respectively). In rats and rabbits, decreased pup/fetal survival occurred at 12 times and equivalent, respectively, to the MRHD of 40 mg/day [see Data].

The estimated background risk of major birth defects and miscarriage for the indicated population is unknown. In the U.S. general population, the estimated background risk of major birth defects and miscarriage in clinically recognized pregnancies is 2-4% and 15-20%, respectively.

Data

Human Data

Limited published data on rosuvastatin have not shown an increased risk of major congenital malformations or miscarriage. Rare reports of congenital anomalies have been received following intrauterine exposure to other statins. In a review of approximately 100 prospectively followed pregnancies in women exposed to simvastatin or lovastatin, the incidences of congenital anomalies, spontaneous abortions, and fetal deaths/stillbirths did not exceed what would be expected in the general population. The number of cases is adequate to exclude a ≥3 to 4-fold increase in congenital anomalies over the background incidence. In 89% of the prospectively followed pregnancies, drug treatment was initiated prior to pregnancy and was discontinued at some point in the first trimester when pregnancy was identified.

Animal Data

Rosuvastatin crosses the placenta in rats and rabbits and is found in fetal tissue and amniotic fluid at 3% and 20%, respectively, of the maternal plasma concentration following a single 25 mg/kg oral gavage dose on gestation day 16 in rats. A higher fetal tissue distribution (25% maternal plasma concentration) was observed in rabbits after a single oral gavage dose of 1 mg/kg on gestation day 18.

Rosuvastatin administration did not indicate a teratogenic effect in rats at ≤25 mg/kg/day or in rabbits ≤3 mg/kg/day (doses equivalent to the MRHD of 40 mg/day based on AUC and body surface area, respectively).

In female rats given 5, 15 and 50 mg/kg/day before mating and continuing through to gestation day 7 resulted in decreased fetal body weight (female pups) and delayed ossification at 50 mg/kg/day (10 times the human exposure at the MRHD dose of 40 mg/day based on AUC).

In pregnant rats given 2, 10 and 50 mg/kg/day of rosuvastatin from gestation day 7 through lactation day 21 (weaning), decreased pup survival occurred at 50 mg/kg/day (dose equivalent to 12 times the MRHD of 40 mg/day based body surface area).

In pregnant rabbits given 0.3, 1, and 3 mg/kg/day of rosuvastatin from gestation day 6 to day 18, decreased fetal viability and maternal mortality was observed at 3 mg/kg/day (dose equivalent to the MRHD of 40 mg/day based on body surface area).

8.2 Lactation

Risk Summary

Rosuvastatin use is contraindicated during breastfeeding [see Contraindications (4)]. Limited data indicate that CRESTOR is present in human milk. There is no available information on the effects of the drug on the breastfed infant or the effects of the drug on milk production. Because of the potential for serious adverse reactions in a breastfed infant, advise patients that breastfeeding is not recommended during treatment with CRESTOR.

8.3 Females and Males of Reproductive Potential

Contraception

CRESTOR may cause fetal harm when administered to a pregnant woman [see Use in Specific Populations (8.1)]. Advise females of reproductive potential to use effective contraception during treatment with CRESTOR.

8.4 Pediatric Use

In children and adolescents 8 to 17 years of age with heterozygous familial hypercholesterolemia, the safety and effectiveness of CRESTOR as an adjunct to diet to reduce total cholesterol, LDL-C, and ApoB levels when, after an adequate trial of diet therapy, LDL-C exceeds 190 mg/dL or when LDL-C exceeds 160 mg/dL and there is a positive family history of premature CVD or two or more other CVD risk factors, were established in one controlled trial and in one open-label, uncontrolled trial [see Clinical Studies (14.7)]. The long-term efficacy of CRESTOR therapy initiated in childhood to reduce morbidity and mortality in adulthood has not been established.

The safety and effectiveness of CRESTOR in children and adolescents 10 to 17 years of age with heterozygous familial hypercholesterolemia were evaluated in a controlled clinical trial of 12 weeks duration followed by 40 weeks of open-label exposure. Patients treated with 5 mg, 10 mg, and 20 mg daily CRESTOR had an adverse experience profile generally similar to that of patients treated with placebo. There was no detectable effect of CRESTOR on growth, weight, BMI (body mass index), or sexual maturation [see Clinical Studies (14.7)] in children and adolescents (10 to 17 years of age).

CRESTOR has not been studied in controlled clinical trials involving prepubertal patients or patients younger than 10 years of age with heterozygous familial hypercholesterolemia. However, the safety and effectiveness of CRESTOR were evaluated in a two year open-label uncontrolled trial that included children and adolescents 8 to 17 years of age with heterozygous familial hypercholesterolemia [see Clinical Studies (14.7)]. The safety and efficacy of CRESTOR in lowering LDL-C appeared generally consistent with that observed for adult patients, despite limitations of the uncontrolled study design.

Children and adolescents 7 to 15 years of age with homozygous familial hypercholesterolemia were studied in a 6-week randomized, placebo-controlled, cross-over study with CRESTOR 20 mg once daily followed by 12 weeks of open-label treatment [see Clinical Studies (14.6)]. In general, the safety profile in this trial was consistent with that of the previously established safety profile in adults.

Although not all adverse reactions identified in the adult population have been observed in clinical trials of children and adolescent patients, the same warnings and precautions for adults should be considered for children and adolescents. Adolescent females should be counseled on appropriate contraceptive methods while on CRESTOR therapy [see Use in Specific Populations (8.1)].

8.5 Geriatric Use

Of the 10,275 patients in clinical studies with CRESTOR, 3159 (31%) were 65 years and older, and 698 (6.8%) were 75 years and older. No overall differences in safety or effectiveness were observed between these subjects and younger subjects, and other reported clinical experience has not identified differences in responses between the elderly and younger patients, but greater sensitivity of some older individuals cannot be ruled out.

Elderly patients are at higher risk of myopathy and CRESTOR should be prescribed with caution in the elderly [see Warnings and Precautions (5.1) and Clinical Pharmacology (12.3)].

8.6 Renal Impairment

Rosuvastatin exposure is not influenced by mild to moderate renal impairment (CLcr ≥30 mL/min/1.73 m^2). Exposure to rosuvastatin is increased to a clinically significant extent in patients with severe renal impairment (CLcr <30 mL/min/1.73 m^2) who are not receiving hemodialysis and dose adjustment is required [see Dosage and Administration (2.5), Warnings and Precautions (5.1) and Clinical Pharmacology (12.3)].

8.7 Hepatic Impairment

CRESTOR is contraindicated in patients with active liver disease, which may include unexplained persistent elevations of hepatic transaminase levels. Chronic alcohol liver disease is known to increase rosuvastatin exposure; CRESTOR should be used with caution in these patients [see Contraindications (4), Warning and Precautions (5.2) and Clinical Pharmacology (12.3)].

8.8 Asian Patients

Pharmacokinetic studies have demonstrated an approximate 2‑fold increase in median exposure to rosuvastatin in Asian subjects when compared with Caucasian controls. CRESTOR dosage should be adjusted in Asian patients [see Dosage and Administration (2.3) and Clinical Pharmacology (12.3)].

10 OVERDOSAGE

There is no specific treatment in the event of overdose. In the event of overdose, the patient should be treated symptomatically and supportive measures instituted as required. Hemodialysis does not significantly enhance clearance of rosuvastatin.

11 DESCRIPTION

CRESTOR (rosuvastatin calcium) is a synthetic lipid-lowering agent for oral administration.

The chemical name for rosuvastatin calcium is bis[(E)-7-[4-(4-fluorophenyl)-6-isopropyl-2-[methyl(methylsulfonyl)amino] pyrimidin-5-yl](3R,5S)-3,5-dihydroxyhept-6-enoic acid] calcium salt with the following structural formula:

The empirical formula for rosuvastatin calcium is (C22H27FN3O6S)2Ca and the molecular weight is 1001.14. Rosuvastatin calcium is a white amorphous powder that is sparingly soluble in water and methanol, and slightly soluble in ethanol. Rosuvastatin calcium is a hydrophilic compound with a partition coefficient (octanol/water) of 0.13 at pH of 7.0.

CRESTOR Tablets for oral administration contain 5, 10, 20, or 40 mg of rosuvastatin and the following inactive ingredients: Each tablet contains: microcrystalline cellulose NF, lactose monohydrate NF, tribasic calcium phosphate NF, crospovidone NF, magnesium stearate NF, hypromellose NF, triacetin NF, titanium dioxide USP, yellow ferric oxide, and red ferric oxide NF.

12 CLINICAL PHARMACOLOGY

12.1 Mechanism of Action

CRESTOR is a selective and competitive inhibitor of HMG-CoA reductase, the rate-limiting enzyme that converts 3‑hydroxy‑3‑methylglutaryl coenzyme A to mevalonate, a precursor of cholesterol. In vivo studies in animals, and in vitro studies in cultured animal and human cells have shown rosuvastatin to have a high uptake into, and selectivity for, action in the liver, the target organ for cholesterol lowering. In in vivo and in vitro studies, rosuvastatin produces its lipid-modifying effects in two ways. First, it increases the number of hepatic LDL receptors on the cell-surface to enhance uptake and catabolism of LDL. Second, rosuvastatin inhibits hepatic synthesis of VLDL, which reduces the total number of VLDL and LDL particles.

12.2 Pharmacodynamics

CRESTOR dose dependently reduces elevated LDL-cholesterol and reduces total cholesterol and triglycerides and increases HDL-cholesterol [see Clinical Studies (14)]. A therapeutic response to CRESTOR is evident within 1 week of commencing therapy and 90% of maximum response is usually achieved in 2 weeks. The maximum response is usually achieved by 4 weeks and is maintained after that. Individualization of drug dosage should be based on the therapeutic response [see Dosage and Administration (2)].

12.3 Pharmacokinetics

Absorption

In clinical pharmacology studies in man, peak plasma concentrations of rosuvastatin were reached 3 to 5 hours following oral dosing. Both Cmax and AUC increased in approximate proportion to CRESTOR dose. The absolute bioavailability of rosuvastatin is approximately 20%.

Administration of CRESTOR with food did not affect the AUC of rosuvastatin.

The AUC of rosuvastatin does not differ following evening or morning drug administration.

Distribution

Mean volume of distribution at steady-state of rosuvastatin is approximately 134 liters. Rosuvastatin is 88% bound to plasma proteins, mostly albumin. This binding is reversible and independent of plasma concentrations.

Elimination

Rosuvastatin is primarily eliminated by excretion in the feces. The elimination half-life of rosuvastatin is approximately 19 hours.

Metabolism

Rosuvastatin is not extensively metabolized; approximately 10% of a radiolabeled dose is recovered as metabolite. The major metabolite is N-desmethyl rosuvastatin, which is formed principally by cytochrome P450 \ 2C9, and in vitro studies have demonstrated that N-desmethyl rosuvastatin has approximately one-sixth to one-half the HMG‑CoA reductase inhibitory activity of the parent compound. Overall, greater than 90% of active plasma HMG‑CoA reductase inhibitory activity is accounted for by the parent compound.

Excretion

Following oral administration, rosuvastatin and its metabolites are primarily excreted in the feces (90%).

After an intravenous dose, approximately 28% of total body clearance was via the renal route, and 72% by the hepatic route.

Specific Populations

Racial or Ethnic Groups

A population pharmacokinetic analysis revealed no clinically relevant differences in pharmacokinetics among Caucasian, Hispanic, and Black or Afro-Caribbean groups. However, pharmacokinetic studies, including one conducted in the US, have demonstrated an approximate 2‑fold elevation in median exposure (AUC and Cmax) in Asian subjects when compared with a Caucasian control group.

Male and Female Patients

There were no differences in plasma concentrations of rosuvastatin between men and women.

Pediatric Patients

In a population pharmacokinetic analysis of two pediatric trials involving patients with heterozygous familial hypercholesterolemia 10 to 17 years of age and 8 to 17 years of age, respectively, rosuvastatin exposure appeared comparable to or lower than rosuvastatin exposure in adult patients.

Geriatric Patients

There were no differences in plasma concentrations of rosuvastatin between the nonelderly and elderly populations (age ≥65 years).

Patients with Renal Impairment

Mild to moderate renal impairment (CLcr ≥30 mL/min/1.73 m^2) had no influence on plasma concentrations of rosuvastatin. However, plasma concentrations of rosuvastatin increased to a clinically significant extent (about 3‑fold) in patients with severe renal impairment (CLcr <30 mL/min/1.73 m^2) not receiving hemodialysis compared with healthy subjects (CLcr >80 mL/min/1.73 m^2).

Hemodialysis

Steady-state plasma concentrations of rosuvastatin in patients on chronic hemodialysis were approximately 50% greater compared with healthy volunteer subjects with normal renal function.

Patients with Hepatic Impairment

In patients with chronic alcohol liver disease, plasma concentrations of rosuvastatin were modestly increased.

In patients with Child‑Pugh A disease, Cmax and AUC were increased by 60% and 5%, respectively, as compared with patients with normal liver function. In patients with Child‑Pugh B disease, Cmax and AUC were increased 100% and 21%, respectively, compared with patients with normal liver function.

Drug Interactions Studies

Rosuvastatin clearance is not dependent on metabolism by cytochrome P450 3A4 to a clinically significant extent.

Rosuvastatin is a substrate for certain transporter proteins including the hepatic uptake transporter organic anion-transporting polyprotein 1B1 (OATP1B1) and efflux transporter breast cancer resistance protein (BCRP). Concomitant administration of CRESTOR with medications that are inhibitors of these transporter proteins (e.g., cyclosporine, certain HIV protease inhibitors) may result in increased rosuvastatin plasma concentrations [see Dosage and Administration (2.4) and Drug Interactions (7.1, 7.3)].

Table 4. Effect of Coadministered Drugs on Rosuvastatin Systemic Exposure
Coadministered drug and dosing regimen | Rosuvastatin
 |  | Mean Ratio (ratio with/without coadministered drug) No Effect=1.0
 | Dose (mg) [Single dose unless otherwise noted.] | Change in AUC | Change in Cmax
Cyclosporine – stable dose required (75 mg – 200 mg BID) | 10 mg QD for 10 days | 7.1 [Clinically significant [see Dosage and Administration (2) and Warnings and Precautions (5)]] | 11
Atazanavir/ritonavir combination 300 mg/100 mg QD for 8 days | 10 mg | 3.1 | 7
Simeprevir 150 mg QD, 7 days | 10 mg, single dose | 2.8; (2.3-3.4) [Mean ratio with 90% CI (with/without coadministered drug, e.g., 1= no change, 0.7 = 30% decrease, 11=11 fold increase in exposure)] | 3.2; (2.6-3.9)
Lopinavir/ritonavir combination 400 mg/100 mg BID for 17 days | 20 mg QD for 7 days | 2.1; (1.7-2.6) | 5; (3.4-6.4)
Gemfibrozil 600 mg BID for 7 days | 80 mg | 1.9; (1.6-2.2) | 2.2; (1.8-2.7)
Eltrombopag 75 mg QD, 5 days | 10 mg | 1.6; (1.4-1.7) | 2; (1.8-2.3)
Darunavir 600 mg/ritonavir 100 mg BID, 7 days | 10 mg QD for 7 days | 1.5; (1.0-2.1) | 2.4; (1.6-3.6)
Tipranavir/ritonavir combination 500 mg/200mg BID for 11 days | 10 mg | 1.4; (1.2-1.6) | 2.2; (1.8-2.7)
Dronedarone 400 mg BID | 10 mg | 1.4
Itraconazole 200 mg QD, 5 days | 10 mg or 80 mg | 1.4; (1.2-1.6); 1.3; (1.1-1.4) | 1.4; (1.2-1.5); 1.2; (0.9-1.4)
Ezetimibe 10 mg QD, 14 days | 10 mg QD for 14 days | 1.2 (0.9-1.6) | 1.2; (0.8-1.6)
Fosamprenavir/ritonavir 700 mg/100 mg BID for 7 days | 10 mg | 1.1 | 1.5
Fenofibrate 67 mg TID for 7 days | 10 mg | ↔ | 1.2; (1.1-1.3)
Rifampicin 450 mg QD, 7 days | 20 mg | ↔
Aluminum & magnesium hydroxide combination antacid; Administered simultaneously Administered 2 hours apart | 40 mg 40 mg | 0.5; (0.4-0.5) 0.8; (0.7-0.9) | 0.5; (0.4-0.6) 0.8; (0.7-1.0)
Ketoconazole 200 mg BID for 7 days | 80 mg | 1.0; (0.8-1.2) | 1.0; (0.7-1.3)
Fluconazole 200 mg QD for 11 days | 80 mg | 1.1; (1.0-1.3) | 1.1; (0.9-1.4)
Erythromycin 500 mg QID for 7 days | 80 mg | 0.8; (0.7-0.9) | 0.7; (0.5-0.9)

Table 5. Effect of Rosuvastatin Coadministration on Systemic Exposure to Other Drugs
Rosuvastatin Dosage Regimen | Coadministered Drug
 |  | Mean Ratio (ratio with/without coadministered drug) No Effect=1.0
 | Name and Dose | Change in AUC | Change in Cmax
40 mg QD for 10 days | Warfarin [Clinically significant pharmacodynamic effects [see Warnings and Precautions (5.3)]]; 25 mg single dose | R- Warfarin 1.0; (1.0-1.1) [Mean ratio with 90% CI (with/without coadministered drug, e.g., 1= no change, 0.7=30% decrease, 11=11-fold increase in exposure)]; S-Warfarin 1.1; (1.0-1.1) | R-Warfarin 1.0; (0.9-1.0); S-Warfarin 1.0; (0.9-1.1)
40 mg QD for 12 days | Digoxin; 0.5 mg single dose | 1.0; (0.9-1.2) | 1.0; (0.9-1.2)
40 mg QD for 28 days | Oral Contraceptive; (ethinyl estradiol 0.035 mg & norgestrel 0.180, 0.215 and 0.250 mg) QD for 21 Days | EE 1.3; (1.2-1.3); NG 1.3; (1.3-1.4) | EE 1.3; (1.2-1.3); NG 1.2; (1.1-1.3)
EE = ethinyl estradiol, NG = norgestrel

12.5 Pharmacogenomics

Disposition of HMG-CoA reductase inhibitors, including rosuvastatin, involves OATP1B1 and other transporter proteins. Higher plasma concentrations of rosuvastatin have been reported in very small groups of patients (n=3 to 5) who have two reduced function alleles of the gene that encodes OATP1B1 (SLCO1B1 521T > C). The frequency of this genotype (i.e., SLCO1B1 521 C/C) is generally lower than 5% in most racial/ethnic groups. The impact of this polymorphism on efficacy and/or safety of rosuvastatin has not been clearly established.

13 NONCLINICAL TOXICOLOGY

13.1 Carcinogenesis, Mutagenesis, Impairment of Fertility

In a 104-week carcinogenicity study in rats at dose levels of 2, 20, 60, or 80 mg/kg/day by oral gavage, the incidence of uterine stromal polyps was significantly increased in females at 80 mg/kg/day at systemic exposure 20 times the human exposure at 40 mg/day based on AUC. Increased incidence of polyps was not seen at lower doses.

In a 107-week carcinogenicity study in mice given 10, 60, or 200 mg/kg/day by oral gavage, an increased incidence of hepatocellular adenoma/carcinoma was observed at 200 mg/kg/day at systemic exposures 20 times the human exposure at 40 mg/day based on AUC. An increased incidence of hepatocellular tumors was not seen at lower doses.

Rosuvastatin was not mutagenic or clastogenic with or without metabolic activation in the Ames test with Salmonella typhimurium and Escherichia coli, the mouse lymphoma assay, and the chromosomal aberration assay in Chinese hamster lung cells. Rosuvastatin was negative in the in vivo mouse micronucleus test.

In rat fertility studies with oral gavage doses of 5, 15, 50 mg/kg/day, males were treated for 9 weeks prior to and throughout mating and females were treated 2 weeks prior to mating and throughout mating until gestation day 7. No adverse effect on fertility was observed at 50 mg/kg/day (systemic exposures up to 10 times the human exposure at 40 mg/day based on AUC). In testicles of dogs treated with rosuvastatin at 30 mg/kg/day for one month, spermatidic giant cells were seen. Spermatidic giant cells were observed in monkeys after 6‑month treatment at 30 mg/kg/day in addition to vacuolation of seminiferous tubular epithelium. Exposures in the dog were 20 times and in the monkey 10 times the human exposure at 40 mg/day based on body surface area. Similar findings have been seen with other drugs in this class.

13.2 Animal Toxicology and/or Pharmacology

Central Nervous System Toxicity

CNS vascular lesions, characterized by perivascular hemorrhages, edema, and mononuclear cell infiltration of perivascular spaces, have been observed in dogs treated with several other members of this drug class. A chemically similar drug in this class produced dose-dependent optic nerve degeneration (Wallerian degeneration of retinogeniculate fibers) in dogs, at a dose that produced plasma drug levels about 30 times higher than the mean drug level in humans taking the highest recommended dose. Edema, hemorrhage, and partial necrosis in the interstitium of the choroid plexus was observed in a female dog sacrificed moribund at day 24 at 90 mg/kg/day by oral gavage (systemic exposures 100 times the human exposure at 40 mg/day based on AUC). Corneal opacity was seen in dogs treated for 52 weeks at 6 mg/kg/day by oral gavage (systemic exposures 20 times the human exposure at 40 mg/day based on AUC). Cataracts were seen in dogs treated for 12 weeks by oral gavage at 30 mg/kg/day (systemic exposures 60 times the human exposure at 40 mg/day based on AUC). Retinal dysplasia and retinal loss were seen in dogs treated for 4 weeks by oral gavage at 90 mg/kg/day (systemic exposures 100 times the human exposure at 40 mg/day based on AUC). Doses ≤30 mg/kg/day (systemic exposures ≤60 times the human exposure at 40 mg/day based on AUC) did not reveal retinal findings during treatment for up to one year.

Juvenile Toxicology Study

In a juvenile study, rats were dosed by oral gavage with 10 or 50 mg/kg/day from weaning for 9 weeks prior to pairing, throughout pairing and up to the day before necropsy for males or up to gestation day 7 for females. No effects on sexual development, testicular and epididymal appearance or fertility were observed at either dose level (2 times or up to 24 times the human exposure (AUC) at the maximum pediatric dose of 20 mg/day).

14 CLINICAL STUDIES

14.1 Hyperlipidemia and Mixed Dyslipidemia

CRESTOR reduces Total‑C, LDL‑C, ApoB, nonHDL‑C, and TG, and increases HDL‑C, in adult patients with hyperlipidemia and mixed dyslipidemia.

Dose-Ranging Study: In a multicenter, double-blind, placebo-controlled, dose-ranging study in patients with hyperlipidemia CRESTOR given as a single daily dose for 6 weeks significantly reduced Total‑C, LDL‑C, nonHDL‑C, and ApoB, across the dose range (Table 6).

Table 6. Dose-Response in Patients with Hyperlipidemia (Adjusted Mean % Change from Baseline at Week 6)
Dose | N | Total‑C | LDL‑C | Non-HDL‑C | ApoB | TG | HDL‑C
Placebo | 13 | -5 | -7 | -7 | -3 | -3 | 3
CRESTOR 5 mg | 17 | -33 | -45 | -44 | -38 | -35 | 13
CRESTOR 10 mg | 17 | -36 | -52 | -48 | -42 | -10 | 14
CRESTOR 20 mg | 17 | -40 | -55 | -51 | -46 | -23 | 8
CRESTOR 40 mg | 18 | -46 | -63 | -60 | -54 | -28 | 10

Active-Controlled Study: CRESTOR was compared with the HMG‑CoA reductase inhibitors atorvastatin, simvastatin, and pravastatin in a multicenter, open-label, dose-ranging study of 2240 patients with hyperlipidemia or mixed dyslipidemia. After randomization, patients were treated for 6 weeks with a single daily dose of either CRESTOR, atorvastatin, simvastatin, or pravastatin (Figure 1 and Table 7).

Figure 1. Percent LDL‑C Change by Dose of CRESTOR, Atorvastatin, Simvastatin, and Pravastatin at Week 6 in Patients with Hyperlipidemia or Mixed Dyslipidemia

Box plots are a representation of the 25th, 50th, and 75th percentile values, with whiskers representing the 10th and 90th percentile values. Mean baseline LDL‑C: 189 mg/dL

Table 7. Percent Change in LDL-C From Baseline to Week 6 (LS Mean [Corresponding standard errors are approximately 1.00.]) by Treatment Group (Sample Sizes Ranging from 156-167 Patients Per Group)
 | Treatment Daily Dose
Treatment | 10 mg | 20 mg | 40 mg | 80 mg
CRESTOR | -46 [CRESTOR 10 mg reduced LDL-C significantly more than atorvastatin 10 mg; pravastatin 10 mg, 20 mg, and 40 mg; simvastatin 10 mg, 20 mg, and 40 mg. (p<0.002)] | -52 [CRESTOR 20 mg reduced LDL-C significantly more than atorvastatin 20 mg and 40 mg; pravastatin 20 mg and 40 mg; simvastatin 20 mg, 40 mg, and 80 mg. (p<0.002)] | -55 [CRESTOR 40 mg reduced LDL-C significantly more than atorvastatin 40 mg; pravastatin 40 mg; simvastatin 40 mg, and 80 mg. (p<0.002)] | ---
Atorvastatin | -37 | -43 | -48 | -51
Simvastatin | -28 | -35 | -39 | -46
Pravastatin | -20 | -24 | -30 | ---

14.2 Heterozygous Familial Hypercholesterolemia

Active-Controlled Study: In a study of patients with heterozygous FH (baseline mean LDL of 291), patients were randomized to CRESTOR 20 mg or atorvastatin 20 mg. The dose was increased by 6-week intervals. Significant LDL-C reductions from baseline were seen at each dose in both treatment groups (Table 8).

Table 8. Mean LDL-C Percentage Change from Baseline
 |  | CRESTOR (n=435) LS Mean [LS Means are least square means adjusted for baseline LDL-C] (95% CI) | Atorvastatin (n=187) LS Mean (95% CI)
Week 6 | 20 mg | -47% (-49%, -46%) | -38% (-40%, -36%)
Week 12 | 40 mg | -55% (-57%, -54%) | -47% (-49%, -45%)
Week 18 | 80 mg | NA | -52% (-54%, -50%)

14.3 Hypertriglyceridemia

Dose-Response Study: In a double-blind, placebo-controlled dose-response study in patients with baseline TG levels from 273 to 817 mg/dL, CRESTOR given as a single daily dose (5 to 40 mg) over 6 weeks significantly reduced serum TG levels (Table 9).

Table 9. Dose-Response in Patients with Primary Hypertriglyceridemia over 6 Weeks Dosing Median (Min, Max) Percent Change from Baseline
Dose | Placebo (n=26) | CRESTOR 5 mg (n=25) | CRESTOR 10 mg (n=23) | CRESTOR 20 mg (n=27) | CRESTOR 40 mg (n=25)
Triglycerides | 1 (-40, 72) | -21 (-58, 38) | -37 (-65, 5) | -37 (-72, 11) | -43 (-80, -7)
nonHDL-C | 2 (-13, 19) | -29 (-43, -8) | -49 (-59, -20) | -43 (-74, 12) | -51 (-62, -6)
VLDL-C | 2 (-36, 53) | -25 (-62, 49) | -48 (-72, 14) | -49 (-83, 20) | -56 (-83, 10)
Total-C | 1 (-13, 17) | -24 (-40, -4) | -40 (-51, -14) | -34 (-61, -11) | -40 (-51, -4)
LDL-C | 5 (-30, 52) | -28 (-71, 2) | -45 (-59, 7) | -31 (-66, 34) | -43 (-61, -3)
HDL-C | -3 (-25, 18) | 3 (-38, 33) | 8 (-8, 24) | 22 (-5, 50) | 17 (-14, 63)

14.4 Primary Dysbetalipoproteinemia (Type III Hyperlipoproteinemia)

In a randomized, multicenter, double-blind crossover study, 32 patients (27 with є2/є2 and 4 with apo E mutation [Arg145Cys] with primary dysbetalipoproteinemia (Type III Hyperlipoproteinemia) entered a 6-week dietary lead-in period on the NCEP Therapeutic Lifestyle Change (TLC) diet. Following dietary lead-in, patients were randomized to a sequence of treatments in conjunction with the TLC diet for 6 weeks each: rosuvastatin 10 mg followed by rosuvastatin 20 mg or rosuvastatin 20 mg followed by rosuvastatin 10 mg. CRESTOR reduced non HDL‑C (primary end point) and circulating remnant lipoprotein levels. Results are shown in the table below.

Table 10. Lipid-modifying Effects of Rosuvastatin 10 mg and 20 mg in Primary Dysbetalipoproteinemia (Type III hyperlipoproteinemia) After Six Weeks by Median Percent Change (95% CI) from Baseline (N=32)
 | Median at Baseline (mg/dL) | Median percent change from baseline (95% CI) CRESTOR 10 mg | Median percent change from baseline (95% CI) CRESTOR 20 mg
Total-C | 342.5 | – 43.3; (-46.9, – 37.5) | -47.6; (-51.6,-42.8)
Triglycerides | 503.5 | -40.1; (-44.9, -33.6) | -43.0; (-52.5, -33.1)
NonHDL-C | 294.5 | -48.2; (-56.7, -45.6) | -56.4; (-61.4, -48.5)
VLDL-C + IDL-C | 209.5 | -46.8; (-53.7, -39.4) | -56.2; (-67.7, -43.7)
LDL-C | 112.5 | -54.4; (-59.1, -47.3) | -57.3; (-59.4, -52.1)
HDL-C | 35.5 | 10.2; (1.9, 12.3) | 11.2; (8.3, 20.5)
RLP-C | 82.0 | -56.4; (-67.1, -49.0) | -64.9; (-74.0, -56.6)
Apo-E | 16.0 | -42.9; (-46.3, -33.3) | -42.5; (-47.1, -35.6)

14.5 Homozygous Familial Hypercholesterolemia

Dose-Titration Study: In an open-label, forced-titration study, homozygous FH patients (n=40, 8‑63 years) were evaluated for their response to CRESTOR 20 to 40 mg titrated at a 6‑week interval. In the overall population, the mean LDL‑C reduction from baseline was 22%. About one-third of the patients benefited from increasing their dose from 20 mg to 40 mg with further LDL lowering of greater than 6%. In the 27 patients with at least a 15% reduction in LDL‑C, the mean LDL-C reduction was 30% (median 28% reduction). Among 13 patients with an LDL‑C reduction of <15%, 3 had no change or an increase in LDL‑C. Reductions in LDL‑C of 15% or greater were observed in 3 of 5 patients with known receptor negative status.

14.6 Pediatric Patients with Homozygous Familial Hypercholesterolemia

CRESTOR was studied in a randomized, double-blind, placebo-controlled, multicenter, cross-over study in 14 children and adolescents with homozygous familial hypercholesterolemia. The study included a 4-week dietary lead-in phase during which patients received CRESTOR 10 mg daily, a cross-over phase that included two 6-week treatment periods with either CRESTOR 20 mg or placebo in random order, followed by a 12-week open-label phase during which all patients received CRESTOR 20 mg. Patients ranged in age from 7 to 15 years of age (median 11 years), 50% were male, 71% were Caucasian, 21% were Asian, 7% were Black, and no patients were of Hispanic ethnicity. Fifty percent were on apheresis therapy and 57% were taking ezetimibe. Patients who entered the study on apheresis therapy or ezetimibe continued the treatment throughout the entire study. Mean LDL-C at baseline was 416 mg/dL (range 152 to 716 mg/dL). A total of 13 patients completed both treatment periods of the randomized cross-over phase; one patient withdrew consent due to inability to have blood drawn during the cross-over phase.

CRESTOR 20 mg significantly reduced LDL-C, total cholesterol, ApoB, and non-HDL-C compared to placebo (Table 11).

Table 11. Lipid-modifying Effects of Rosuvastatin in Pediatric Patients 7 to 15 years of Age with Homozygous Familial Hypercholesterolemia After 6 Weeks
 | Placebo; (N=13) | CRESTOR 20 mg; (N=13) | Percent difference (95% CI)
LDL-C (mg/dL) | 481 | 396 | -22.3% (-33.5, -9.1) [p=0.005]
Total-C (mg/dL) | 539 | 448 | -20.1% (-29.7, -9.1) [p=0.003]
Non-HDL-C (mg/dL) | 505 | 412 | -22.9% (-33.7, ‑10.3)
ApoB (mg/dL) | 268 | 235 | -17.1% (-29.2, -2.9) [p=0.024]
% Difference estimates are based on transformations of the estimated mean difference in log LDL measurements between CRESTOR and placebo using a mixed model adjusted for study period

14.7 Pediatric Patients with Heterozygous Familial Hypercholesterolemia

In a double-blind, randomized, multicenter, placebo-controlled, 12-week study, 176 (97 male and 79 female) children and adolescents with heterozygous familial hypercholesterolemia were randomized to rosuvastatin 5, 10 or 20 mg or placebo daily. Patients ranged in age from 10 to 17 years (median age of 14 years) with approximately 30% of the patients 10 to 13 years and approximately 17%, 18%, 40%, and 25% at Tanner stages II, III, IV, and V, respectively. Females were at least 1 year postmenarche. Mean LDL-C at baseline was 233 mg/dL (range of 129 to 399). The 12-week double-blind phase was followed by a 40-week open label dose-titration phase, where all patients (n=173) received 5 mg, 10 mg or 20 mg rosuvastatin daily.

Rosuvastatin significantly reduced LDL-C (primary end point), total cholesterol and ApoB levels at each dose compared to placebo. Results are shown in Table 12 below.

Table 12. Lipid-Modifying Effects of Rosuvastatin in Pediatric Patients 10 to 17 years of Age with Heterozygous Familial Hypercholesterolemia (Least-Squares Mean Percent Change from Baseline to Week 12)
Dose (mg) | N | LDL-C | HDL-C | Total-C | TG [Median percent change] | ApoB
Placebo | 46 | -1% | +7% | 0% | -7% | -2%
5 | 42 | -38% | +4% [Difference from placebo not statistically significant] | -30% | -13% | -32%
10 | 44 | -45% | +11% | -34% | -15% | -38%
20 | 44 | -50% | +9% | -39% | 16% | -41%

At the end of the 12-week, double-blind treatment period, the percentage of patients achieving the LDL-C goal of less than 110 mg/dL (2.8 mmol/L) was 0% for placebo, 12% for rosuvastatin 5 mg, 41% for rosuvastatin 10 mg and 41% for rosuvastatin 20 mg. For the 40-week, open-label phase, 71% of the patients were titrated to the maximum dose of 20 mg and 41% of the patients achieved the LDL-C goal of 110 mg/dL.

Rosuvastatin was also studied in a two year open-label, uncontrolled, titration to goal trial that included 175 children and adolescents with heterozygous familial hypercholesterolemia who were 8 to 17 years old (79 boys and 96 girls). All patients had a documented genetic defect in the LDL receptor or in ApoB. Approximately 89% were Caucasian, 7% were Asian, 1% were Black, and fewer than 1% were Hispanic. Mean LDL-C at baseline was 236 mg/dL. Fifty-eight (33%) patients were prepubertal at baseline. The starting rosuvastatin dosage for all children and adolescents was 5 mg once daily. Children 8 to less than 10 years of age (n=41 at baseline) could titrate to a maximum dosage of 10 mg once daily, and children and adolescents 10 to 17 years of age could titrate to a maximum dosage of 20 mg once daily.

The reductions in LDL-C from baseline were generally consistent across age groups within the trial as well as with previous experience in both adult and pediatric controlled trials.

The long-term efficacy of rosuvastatin therapy initiated in childhood to reduce morbidity and mortality in adulthood has not been established.

14.8 Slowing of the Progression of Atherosclerosis

In the Measuring Effects on Intima Media Thickness: an Evaluation Of Rosuvastatin 40 mg (METEOR) study, the effect of therapy with CRESTOR on carotid atherosclerosis was assessed by B-mode ultrasonography in patients with elevated LDL‑C, at low risk (Framingham risk <10% over ten years) for symptomatic coronary artery disease and with subclinical atherosclerosis as evidenced by carotid intimal-medial thickness (cIMT). In this double-blind, placebo-controlled clinical study 984 patients were randomized (of whom 876 were analyzed) in a 5:2 ratio to CRESTOR 40 mg or placebo once daily. Ultrasonograms of the carotid walls were used to determine the annualized rate of change per patient from baseline to two years in mean maximum cIMT of 12 measured segments. The estimated difference in the rate of change in the maximum cIMT analyzed over all 12 carotid artery sites between patients treated with CRESTOR and placebo-treated patients was -0.0145 mm/year (95% CI –0.0196, –0.0093; p<0.0001).

The annualized rate of change from baseline for the placebo group was +0.0131 mm/year (p<0.0001). The annualized rate of change from baseline for the group treated with CRESTOR was -0.0014 mm/year (p=0.32).

At an individual patient level in the group treated with CRESTOR, 52.1% of patients demonstrated an absence of disease progression (defined as a negative annualized rate of change), compared to 37.7% of patients in the placebo group.

14.9 Primary Prevention of Cardiovascular Disease

In the Justification for the Use of Statins in Primary Prevention: An Intervention Trial Evaluating Rosuvastatin (JUPITER) study, the effect of CRESTOR (rosuvastatin calcium) on the occurrence of major cardiovascular (CV) disease events was assessed in 17,802 men (≥50 years) and women (≥60 years) who had no clinically evident cardiovascular disease, LDL‑C levels <130 mg/dL (3.3 mmol/l) and hs‑CRP levels ≥2 mg/L. The study population had an estimated baseline coronary heart disease risk of 11.6% over 10 years based on the Framingham risk criteria and included a high percentage of patients with additional risk factors such as hypertension (58%), low HDL‑C levels (23%), cigarette smoking (16%), or a family history of premature CHD (12%). Study participants had a median baseline LDL‑C of 108 mg/dL and hsCRP of 4.3 mg/L. Study participants were randomly assigned to placebo (n=8901) or rosuvastatin 20 mg once daily (n=8901) and were followed for a mean duration of 2 years. The JUPITER study was stopped early by the Data Safety Monitoring Board due to meeting predefined stopping rules for efficacy in rosuvastatin-treated subjects.

The primary end point was a composite end point consisting of the time-to-first occurrence of any of the following major CV events: CV death, nonfatal myocardial infarction, nonfatal stroke, hospitalization for unstable angina or an arterial revascularization procedure.

Rosuvastatin significantly reduced the risk of major CV events (252 events in the placebo group vs. 142 events in the rosuvastatin group) with a statistically significant (p<0.001) relative risk reduction of 44% and absolute risk reduction of 1.2% (see Figure 2). The risk reduction for the primary end point was consistent across the following predefined subgroups: age, sex, race, smoking status, family history of premature CHD, body mass index, LDL‑C, HDL‑C, and hsCRP levels.

Figure 2. Time to First Occurrence of Major Cardiovascular Events in JUPITER

The individual components of the primary end point are presented in Figure 3. Rosuvastatin significantly reduced the risk of nonfatal myocardial infarction, nonfatal stroke, and arterial revascularization procedures. There were no significant treatment differences between the rosuvastatin and placebo groups for death due to cardiovascular causes or hospitalizations for unstable angina.

Rosuvastatin significantly reduced the risk of myocardial infarction (6 fatal events and 62 nonfatal events in placebo-treated subjects vs. 9 fatal events and 22 nonfatal events in rosuvastatin-treated subjects) and the risk of stroke (6 fatal events and 58 nonfatal events in placebo-treated subjects vs. 3 fatal events and 30 nonfatal events in rosuvastatin-treated subjects).

In a post-hoc subgroup analysis of JUPITER subjects (n=1405; rosuvastatin=725, placebo=680) with a hsCRP ≥2 mg/L and no other traditional risk factors (smoking, BP ≥140/90 or taking antihypertensives, low HDL‑C) other than age, after adjustment for high HDL‑C, there was no significant treatment benefit with rosuvastatin treatment.

Figure 3. Major CV Events by Treatment Group in JUPITER

At one year, rosuvastatin increased HDL‑C and reduced LDL‑C, hsCRP, total cholesterol and serum triglyceride levels (p<0.001 for all versus placebo).

16 HOW SUPPLIED/STORAGE AND HANDLING

Product: 50090-1097

NDC: 50090-1097-1 30 TABLET, FILM COATED in a BOTTLE, PLASTIC

17 PATIENT COUNSELING INFORMATION

Advise the patient to read the FDA-approved patient labeling (Patient Information).

Patients should be instructed not to take 2 doses of CRESTOR within 12 hours of each other.

Skeletal Muscle Effects

Patients should be advised to report promptly unexplained muscle pain, tenderness, or weakness, particularly if accompanied by malaise or fever or if these muscle signs or symptoms persist after discontinuing CRESTOR.

Concomitant Use of Antacids

When taking CRESTOR with an aluminum and magnesium hydroxide combination antacid, the antacid should be taken at least 2 hours after CRESTOR administration.

Embryofetal Toxicity

Advise females of reproductive potential of the risk to a fetus, to use effective contraception during treatment, and to inform their healthcare provider of a known or suspected pregnancy [see Contraindications (4) and Use in Specific Populations (8.1, 8.3)].

Lactation

Advise women not to breastfeed during treatment with CRESTOR [see Contraindications (4) and Use in Specific Populations (8.2)].

Liver Enzymes

It is recommended that liver enzyme tests be performed before the initiation of CRESTOR and if signs or symptoms of liver injury occur. All patients treated with CRESTOR should be advised to promptly report any symptoms that may indicate liver injury, including fatigue, anorexia, right upper abdominal discomfort, dark urine or jaundice.

CRESTOR is a trademark of the AstraZeneca group of companies.

© AstraZeneca 2018

Licensed from SHIONOGI & CO., LTD., Osaka, Japan

Distributed by:

AstraZeneca Pharmaceuticals LP

Wilmington, DE 19850

PATIENT INFORMATION

CRESTOR® (Kres-tor)

rosuvastatin calcium

Tablets

Read this Patient Information carefully before you start taking CRESTOR and each time you get a refill. If you have any questions about CRESTOR, ask your doctor. Only your doctor can determine if CRESTOR is right for you.

What is CRESTOR?

CRESTOR is a prescription medicine that contains a cholesterol-lowering medicine called rosuvastatin calcium. Most of the cholesterol in your blood is made in the liver. CRESTOR works by reducing cholesterol in two ways: CRESTOR blocks an enzyme in the liver causing the liver to make less cholesterol, and CRESTOR increases the uptake and breakdown by the liver of cholesterol already in the blood.

- CRESTOR is used along with diet to:
  - lower the level of your “bad” cholesterol (LDL)
  - increase the level of your “good” cholesterol (HDL)
  - lower the level of fat in your blood (triglycerides)
  - slow the buildup of fatty deposits (plaque) in the walls of blood vessels
- CRESTOR is used to treat:
  - adults who cannot control their cholesterol levels by diet and exercise alone
  - children 8 to 17 years of age with heterozygous familial hypercholesterolemia (an inherited condition that causes high levels of LDL)
  - children 7 to 17 years of age with homozygous familial hypercholesterolemia (an inherited condition that causes high levels of LDL).

CRESTOR is not approved for use in children with heterozygous familial hypercholesterolemia younger than 8 years of age or for use in children with homozygous familial hypercholesterolemia younger than 7 years of age.

CRESTOR is used to reduce the risk of heart attacks and strokes in men 50 years of age and older and women 60 years of age and older who do not have known heart disease but do have certain additional risk factors.

It is not known if CRESTOR is safe and effective in people who have Fredrickson Type I and V dyslipidemias.

Who should not take CRESTOR?

Do not take CRESTOR if you:

- are allergic to rosuvastatin calcium or any of the ingredients in CRESTOR. See the end of this leaflet for a complete list of ingredients in CRESTOR.
- have liver problems.
- are pregnant or think you may be pregnant, or are planning to become pregnant. CRESTOR may harm your unborn baby. If you become pregnant, stop taking CRESTOR and call your doctor right away. If you are not planning to become pregnant you should use effective birth control (contraception) while you are taking CRESTOR.
- are breastfeeding. Medicines like CRESTOR can pass into your breast milk and may harm your baby.

What should I tell my doctor before and while taking CRESTOR?

Tell your doctor if you:

- have unexplained muscle aches or weakness
- have or have had kidney problems
- have or have had liver problems
- drink more than 2 glasses of alcohol daily
- have thyroid problems
- are 65 years of age or older
- are of Asian descent
- are pregnant or think you may be pregnant, or are planning to become pregnant
- are breastfeeding

Tell your doctor about all the medicines you take, including prescription and over-the-counter medicines, vitamins, and herbal supplements.

Talk to your doctor before you start taking any new medicines.

Taking CRESTOR with certain other medicines may affect each other causing side effects. CRESTOR may affect the way other medicines work, and other medicines may affect how CRESTOR works.

Especially tell your doctor if you take:

- cyclosporine (a medicine for your immune system)
- gemfibrozil (a fibric acid medicine for lowering cholesterol)
- anti‑viral medicines including HIV or hepatitis C protease inhibitors (such as lopinavir, ritonavir, fosamprenavir, tipranavir, atazanavir, or simeprevir)
- certain anti-fungal medicines (such as itraconazole, ketoconazole and fluconazole)
- coumarin anticoagulants (medicines that prevent blood clots, such as warfarin)
- niacin or nicotinic acid
- fibric acid derivatives (such as fenofibrate)
- colchicine (a medicine used to treat gout)

Ask your doctor or pharmacist for a list of these medicines if you are not sure.

Know all of the medicines you take. Keep a list of them to show your doctor and pharmacist when you get new medicine.

How should I take CRESTOR?

- Take CRESTOR exactly as your doctor tells you to take it.
- Take CRESTOR, by mouth, 1 time each day. Swallow the tablet whole.
- CRESTOR can be taken at any time of day, with or without food.
- Do not change your dose or stop CRESTOR without talking to your doctor, even if you are feeling well.
- Your doctor may do blood tests to check your cholesterol levels before and during your treatment with CRESTOR. Your doctor may change your dose of CRESTOR if needed.
- Your doctor may start you on a cholesterol lowering diet before giving you CRESTOR. Stay on this diet when you take CRESTOR.
- Wait at least 2 hours after taking CRESTOR to take an antacid that contains a combination of aluminum and magnesium hydroxide.
- If you miss a dose of CRESTOR, take it as soon as you remember. However, do not take 2 doses of CRESTOR within 12 hours of each other.
- If you take too much CRESTOR or overdose, call your doctor or go to the nearest hospital emergency room right away.

What are the Possible Side Effects of CRESTOR?

CRESTOR may cause serious side effects, including:

- Muscle pain, tenderness and weakness (myopathy). Muscle problems, including muscle breakdown, can be serious in some people and rarely cause kidney damage that can lead to death. Tell your doctor right away if:
  - you have unexplained muscle pain, tenderness, or weakness, especially if you have a fever or feel more tired than usual, while you take CRESTOR.
  - you have muscle problems that do not go away even after your doctor has told you to stop taking CRESTOR. Your doctor may do further tests to diagnose the cause of your muscle problems.
Your chances of getting muscle problems are higher if you:
  1. are taking certain other medicines while you take CRESTOR
  2. are 65 years of age or older
  3. have thyroid problems (hypothyroidism) that are not controlled
  4. have kidney problems
  5. are taking higher doses of CRESTOR
- Liver problems. Your doctor should do blood tests to check your liver before you start taking CRESTOR and if you have symptoms of liver problems while you take CRESTOR. Call your doctor right away if you have any of the following symptoms of liver problems:
  - feel unusually tired or weak
  - loss of appetite
  - upper belly pain
  - dark urine
  - yellowing of your skin or the whites of your eyes

The most common side effects may include: headache, muscle aches and pains, abdominal pain, weakness, and nausea.

Additional side effects that have been reported with CRESTOR include memory loss and confusion.

Tell your doctor if you have any side effect that bothers you or that does not go away.

These are not all the possible side effects of CRESTOR. For more information, ask your doctor or pharmacist.

Call your doctor for medical advice about side effects. You may report side effects to FDA at 1-800-FDA-1088.

How should I store CRESTOR?

- Store CRESTOR at room temperature, between 68°F to 77°F (20°C to 25°C) and in a dry place.
- Safely throw away medicine that is out of date or no longer needed.

Keep CRESTOR and all medicines out of the reach of children.

What are the Ingredients in CRESTOR?

Active Ingredient: rosuvastatin as rosuvastatin calcium

Inactive Ingredients: microcrystalline cellulose NF, lactose monohydrate NF, tribasic calcium phosphate NF, crospovidone NF, magnesium stearate NF, hypromellose NF, triacetin NF, titanium dioxide USP, yellow ferric oxide, and red ferric oxide NF.

General Information about the safe and effective use of CRESTOR

Medicines are sometimes prescribed for purposes other than those listed in a Patient Information leaflet. Do not use CRESTOR for a condition for which it was not prescribed. Do not give CRESTOR to other people, even if they have the same medical condition you have. It may harm them.

You can ask your pharmacist or doctor for information about CRESTOR that is written for health professionals.

CRESTOR is a trademark of the AstraZeneca group of companies.

© AstraZeneca 2018

Licensed from SHIONOGI & CO., LTD., Osaka, Japan

Distributed by:

AstraZeneca Pharmaceuticals LP

Wilmington, DE 19850

For more information, go to the CRESTOR website at www.crestor.com or call 1-800-CRESTOR.

This Patient Information has been approved by the U.S. Food and Drug Administration Revised 11/2018